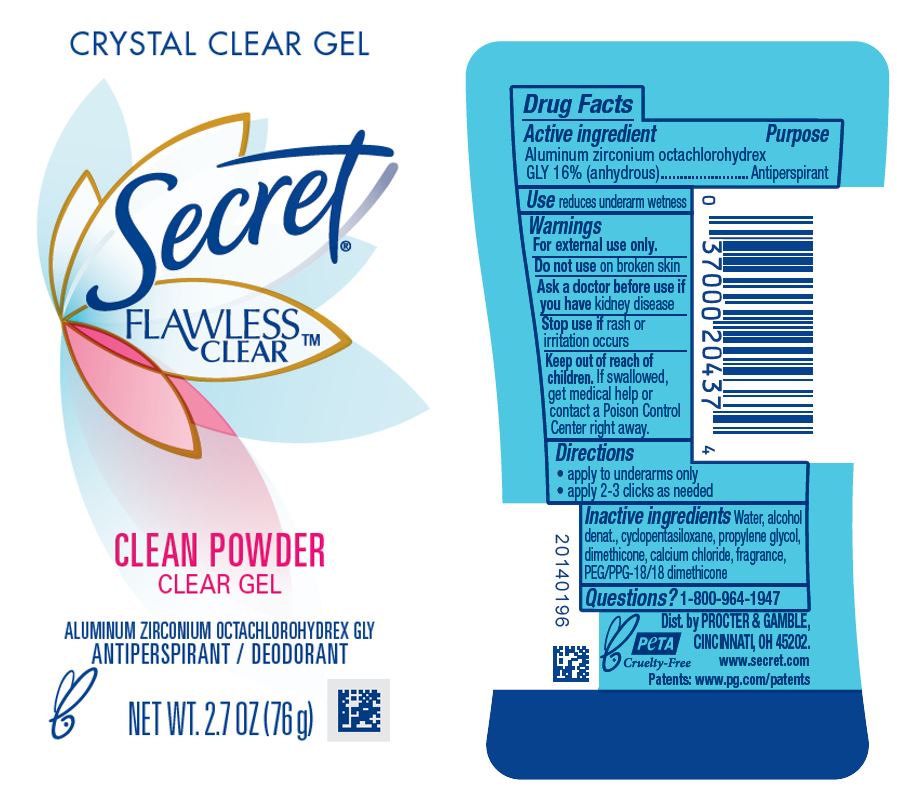 DRUG LABEL: Secret Crystal Clear Flawless Clear Clean
NDC: 84126-028 | Form: GEL
Manufacturer: The Procter & Gamble Manufacturing Company
Category: otc | Type: HUMAN OTC DRUG LABEL
Date: 20251231

ACTIVE INGREDIENTS: ALUMINUM ZIRCONIUM OCTACHLOROHYDREX GLY 16 g/100 g
INACTIVE INGREDIENTS: PEG/PPG-18/18 DIMETHICONE; CALCIUM CHLORIDE; WATER; ALCOHOL; CYCLOMETHICONE 5; PROPYLENE GLYCOL; DIMETHICONE

Secret Crystal Clear Flawless Clear Clean

Drug Facts

Active ingredient

Aluminum zirconium octachlorohydrex Gly 16% (anhydrous)

Purpose

Antiperspirant

Use

reduces underarm wetness

Warnings

For external use only.

Do not use on broken skin

Ask a doctor before use if you have kidney disease

Stop use if rash or irritation occurs

Keep out of reach of children. If swallowed, get medical help or contact a Poison Control Center right away.

Directions

- apply to underarms only
- apply 2-3 clicks as needed

Inactive ingredients

water, alcohol denat., cyclopentasiloxane, propylene glycol, dimethicone, calcium chloride, fragrance, PEG/PPG-18/18 dimethicone

Questions?

1-800-964-1947

Dist. By PROCTER & GAMBLE,
CINCINNATI, OH 45202.

PACKAGE LABEL

CRYSTAL CLEAR GEL

SECRET

FLAWLESS CLEARTM

CLEAN POWDER

CLEAR GEL

ALUMINUM ZIRCONIUM OCTACHLOROHYDREX GLY

ANTIPERSPIRANT / DEODORANT

NET WT. 2.7 OZ (76 g)